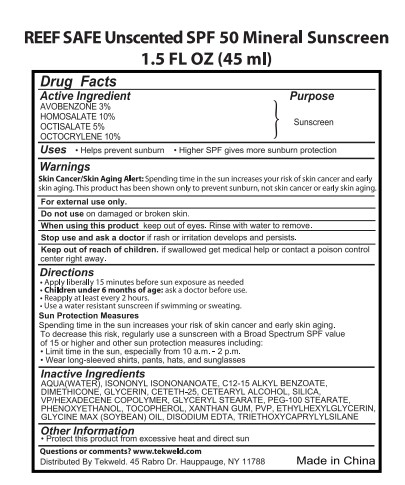 DRUG LABEL: REEF SAFE Unscented SPF Mineral Sunscreen
NDC: 82953-027 | Form: CREAM
Manufacturer: Cosmuses Cosmetics (Ningbo) Co., Ltd.
Category: otc | Type: HUMAN OTC DRUG LABEL
Date: 20241203

ACTIVE INGREDIENTS: OCTOCRYLENE 10 g/100 mL; HOMOSALATE 10 g/100 mL; AVOBENZONE 3 g/100 mL; OCTISALATE 5 g/100 mL
INACTIVE INGREDIENTS: GLYCERIN; VP/HEXADECENE COPOLYMER; TOCOPHEROL; PVP; GLYCINE MAX (SOYBEAN) OIL; ISONONYL ISONONANOATE; PHENOXYETHANOL; CETOSTEARYL ALCOHOL; CETETH-25; EDETATE DISODIUM; PEG-100 STEARATE; WATER; GLYCERYL STEARATE SE; ALKYL (C12-15) BENZOATE; TRIETHOXYCAPRYLYLSILANE; DIMETHICONE; XANTHAN GUM; ETHYLHEXYLGLYCERIN; SILICA

REEF SAFE Unscented SPF 50 Mineral Sunscreen

Drug Facts

Active ingredients

Avobenzone 3%

Homosalate 10%

Octocrylene 10%

Octisalate 5%

Purpose

Sunscreen

Uses

- Helps prevent sunburn
- Higher SPF giwes more sunburn protection

Warnings

For external use only

Skin Cancer/Skin Aging Alert:

Spending time in the sun increases your risk of skin cancer and early skin aging. This product has been shown only to prevent sumburn, not skin cancer or early skin aging.

WARNINGS

For external use only

Do not use on damaged or broken skin.

When using this product keep out of eyes. Rinse with water to remove.

Stop use and ask a doctor if rash or irritation develops and persists.

Keep out of reach of children. If swallowed get medical help or contact a poison control center right away.

Directions

- apply liberally 15minutes before sun exposure as needed
- Children under 6 months of age: ask a doctor before use.
- reapply at least every 2 hours.
- use a water resistant sunscreen if swimming or sweating.

Sun Protection Measures

Spending time in the sun increases your risk of skin cancer and early skin aging.

To decreases this risk, regularly use a sunscreen with a Broad Spectrum SPF value of 15 or higher and other sun protection measures including:

- limit time in the sun, especially from 10a.m.- 2p.m.
- wear long-sleeve shirts, pants, hats and sunglasses

Inactive ingredients

AQUA(WATER), ISONONYL ISONONANOATE, C12-15 ALKYL BENZOATE, DIMETHICONE, GLYCERIN, CETETH-25, CETEARYL ALCOHOL, SILICA, VP/HEXADECENE COPOLYMER, GLYCERYL STEARATE, PEG-100 STEARATE, PHENOXYETHANOL, TOCOPHEROL, XANTHAN GUM, PVP, ETHYLHEXYLGLYCERIN, GLYCINE MAX (SOYBEAN) OIL, DISODIUM EDTA, TRIETHOXYCAPRYLYLSILANE

Other information

Protect this product from excessive heat and direct sun